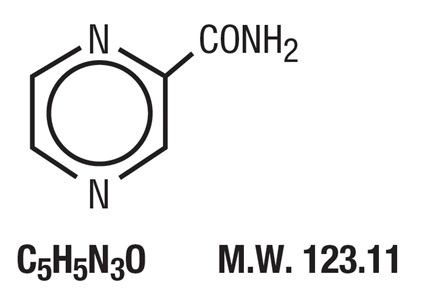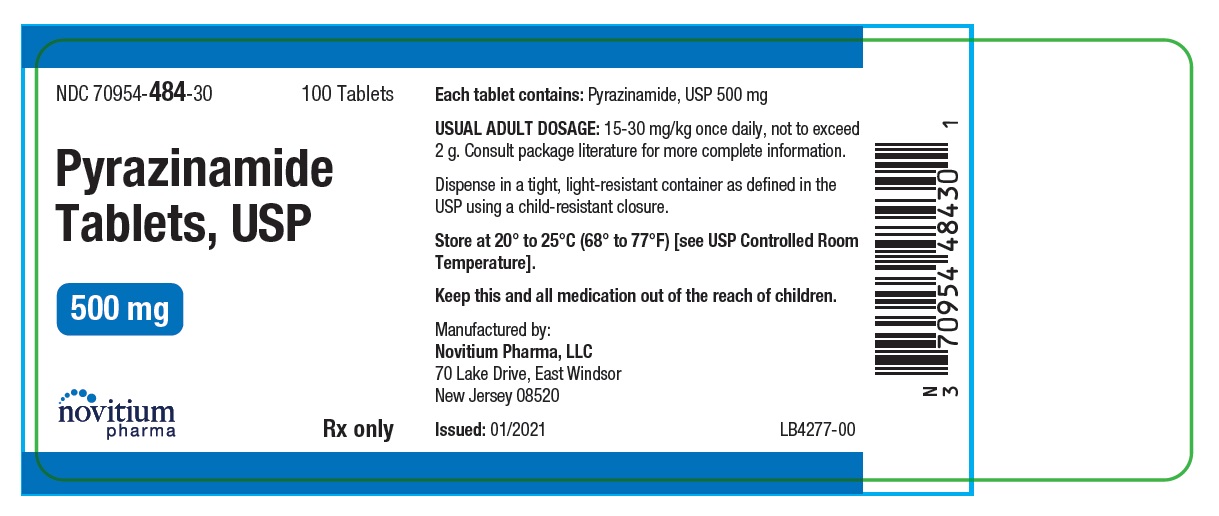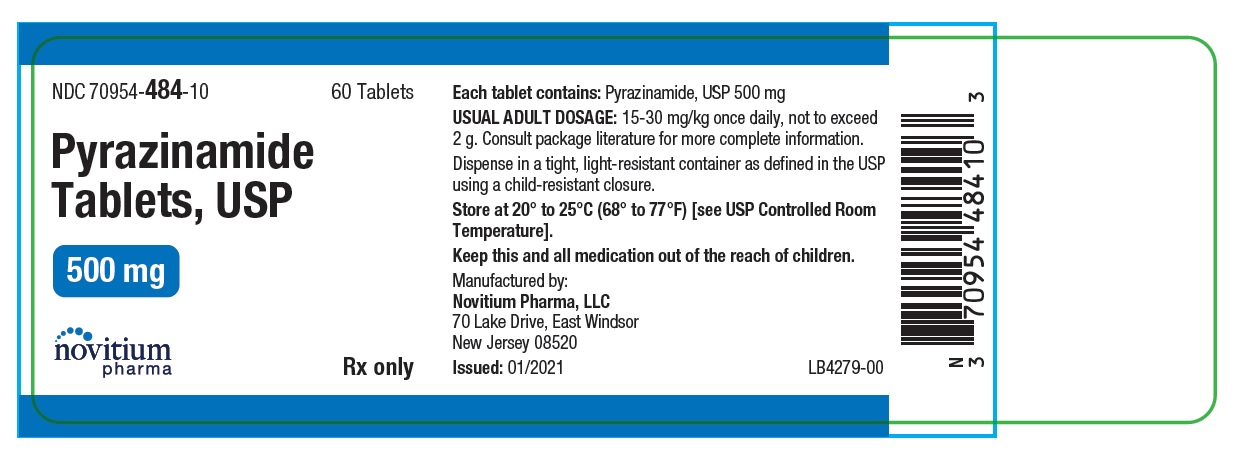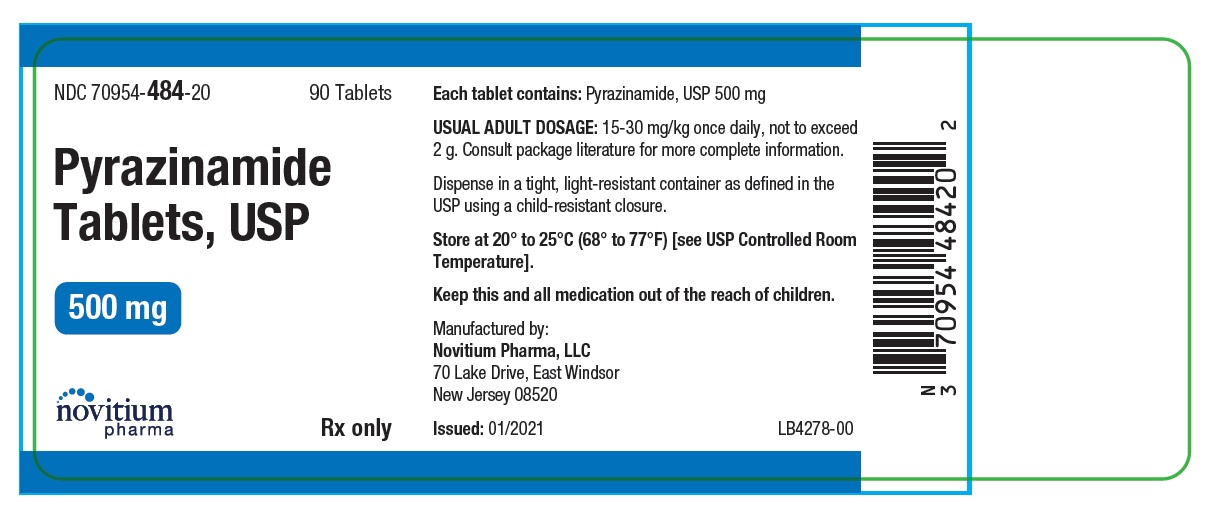 DRUG LABEL: Pyrazinamide
NDC: 70954-484 | Form: TABLET
Manufacturer: ANI Pharmaceuticals, Inc.
Category: prescription | Type: Human Prescription Drug Label
Date: 20260302

ACTIVE INGREDIENTS: PYRAZINAMIDE 500 mg/1 1
INACTIVE INGREDIENTS: STARCH, CORN; MAGNESIUM STEARATE; STEARIC ACID

Pyrazinamide Tablets, USP 500 mg
Rx Only

DESCRIPTION

Pyrazinamide, the pyrazine analogue of nicotinamide, is an antituberculous agent. It is a white crystalline powder, stable at room temperature, and sparingly soluble in water. Pyrazinamide has the following structural formula:
Each pyrazinamide tablet for oral administration contains 500 mg of pyrazinamide and the following inactive ingredients: Corn Starch, Magnesium Stearate, Pregelatinized Starch and Stearic Acid.

CLINICAL PHARMACOLOGY

Pyrazinamide is well absorbed from the GI tract and attains peak plasma concentrations within 2 hours. Plasma concentrations generally range from 30 to 50 mcg/mL with doses of 20 to 25 mg/kg. It is widely distributed in body tissues and fluids including the liver, lungs and cerebrospinal fluid (CSF). The CSF concentration is approximately equal to concurrent steady-state plasma concentrations in patients with inflamed meninges.^1 Pyrazinamide is approximately 10% bound to plasma proteins.^2 The half-life (t1/2) of pyrazinamide is 9 to 10 hours in patients with normal renal and hepatic function. The plasma half-life may be prolonged in patients with impaired renal or hepatic function. Pyrazinamide is hydrolyzed in the liver to its major active metabolite, pyrazinoic acid. Pyrazinoic acid is hydroxylated to the main excretory product, 5-hydroxypyrazinoic acid.^3

Approximately 70% of an oral dose is excreted in urine, mainly by glomerular filtration within 24 hours.^3

Pyrazinamide may be bacteriostatic or bactericidal against Mycobacterium tuberculosis depending on the concentration of the drug attained at the site of infection. The mechanism of action is unknown. In vitro and in vivo the drug is active only at a slightly acidic pH.

INDICATIONS & USAGE

Pyrazinamide is indicated for the initial treatment of active tuberculosis in adults and children when combined with other antituberculous agents. (The current recommendation of the CDC for drug-susceptible disease is to use a six-month regimen for initial treatment of active tuberculosis, consisting of isoniazid, rifampin and pyrazinamide given for 2 months, followed by isoniazid and rifampin for 4 months. *4)

(Patients with drug-resistant disease should be treated with regimens individualized to their situation. Pyrazinamide frequently will be an important component of such therapy.)

(In patients with concomitant HIV infection, the physician should be aware of current recommendations of CDC. It is possible these patients may require a longer course of treatment.)

It is also indicated after treatment failure with other primary drugs in any form of active tuberculosis.

Pyrazinamide should only be used in conjunction with other effective antituberculous agents.

*See recommendations of Center for Disease Control (CDC) and American Thoracic Society for complete regimen and dosage recommendations.^4

CONTRAINDICATIONS

Pyrazinamide is contraindicated in persons:

- with severe hepatic damage.
- who have shown hypersensitivity to it.
- with acute gout.

WARNINGS

Patients started on pyrazinamide should have baseline serum uric acid and liver function determinations. Those patients with preexisting liver disease or those at increased risk for drug related hepatitis (e.g., alcohol abusers) should be followed closely.

Pyrazinamide should be discontinued and not be resumed if signs of hepatocellular damage or hyperuricemia accompanied by an acute gouty arthritis appear.

PRECAUTIONS

GENERAL PRECAUTIONS

Pyrazinamide inhibits renal excretion of urates, frequently resulting in hyperuricemia which is usually asymptomatic. If hyperuricemia is accompanied by acute gouty arthritis, pyrazinamide should be discontinued.

Pyrazinamide should be used with caution in patients with a history of diabetes mellitus, as management may be more difficult.

Primary resistance of M. tuberculosis to pyrazinamide is uncommon. In cases with known or suspected drug resistance, in vitro susceptibility tests with recent cultures of M. tuberculosis against pyrazinamide and the usual primary drugs should be performed. There are few reliable in vitro tests for pyrazinamide resistance. A reference laboratory capable of performing these studies must be employed.

INFORMATION FOR PATIENTS

Patients should be instructed to notify their physicians promptly if they experience any of the following: fever, loss of appetite, malaise, nausea and vomiting, darkened urine, yellowish discoloration of the skin and eyes, pain or swelling of the joints.

Compliance with the full course of therapy must be emphasized, and the importance of not missing any doses must be stressed.

LABORATORY TESTS

Baseline liver function studies [especially ALT (SGPT), AST (SGOT) determinations] and uric acid levels should be determined prior to therapy. Appropriate laboratory testing should be performed at periodic intervals and if any clinical signs or symptoms occur during therapy.

DRUG & OR LABORATORY TEST INTERACTIONS

Pyrazinamide has been reported to interfere with ACETEST® and KETOSTIX® urine tests to produce a pink-brown color.^5

CARCINOGENESIS & MUTAGENESIS & IMPAIRMENT OF FERTILITY

In lifetime bioassays in rats and mice, pyrazinamide was administered in the diet at concentrations of up to 10,000 ppm. This resulted in estimated daily doses for the mouse of 2 g/kg, or 40 times the maximum human dose, and for the rat of 0.5 g/kg, or 10 times the maximum human dose. Pyrazinamide was not carcinogenic in rats or male mice and no conclusion was possible for female mice due to insufficient numbers of surviving control mice.

Pyrazinamide was not mutagenic in the Ames bacterial test, but induced chromosomal aberrations in human lymphocyte cell cultures.

PREGNANCY

Teratogenic Effects – Pregnancy Category C

Animal reproduction studies have not been conducted with pyrazinamide. It is also not known whether pyrazinamide can cause fetal harm when administered to a pregnant woman or can affect reproduction capacity. Pyrazinamide should be given to a pregnant woman only if clearly needed.

NURSING MOTHERS

Pyrazinamide has been found in small amounts in breast milk. Therefore, it is advised that pyrazinamide be used with caution in nursing mothers taking into account the risk-benefit of this therapy.^9

PEDIATRIC USE

Pyrazinamide regimens employed in adults are probably equally effective in pediatric patients.^(4, 10, 11) Pyrazinamide appears to be well tolerated in pediatric patients.

GERIATRIC USE

Clinical studies of pyrazinamide did not include sufficient numbers of patients aged 65 and over to determine whether they respond differently from younger patients. Other reported clinical experience has not identified differences in responses between the elderly and younger patients. In general, dose selection for an elderly patient should be cautious, usually starting at the low end of the dosing range, reflecting the greater frequency of decreased hepatic or renal function, and of concomitant disease or other drug therapy.

It does not appear that patients with impaired renal function require a reduction in dose. It may be prudent to select doses at the low end of the dosing range, however.^13

ADVERSE REACTIONS

General

Fever, porphyria and dysuria have rarely been reported. Gout (see PRECAUTIONS).

Gastrointestinal

The principal adverse effect is a hepatic reaction (see WARNINGS). Hepatotoxicity appears to be dose related, and may appear at any time during therapy. GI disturbances including nausea, vomiting and anorexia have also been reported.

Hematologic and Lymphatic

Thrombocytopenia and sideroblastic anemia with erythroid hyperplasia, vacuolation of erythrocytes and increased serum iron concentration have occurred rarely with this drug. Adverse effects on blood clotting mechanisms have also been rarely reported.

Other

Mild arthralgia and myalgia have been reported frequently. Hypersensitivity reactions including rashes, urticaria, and pruritus have been reported. Fever, acne, photosensitivity, porphyria, dysuria and interstitial nephritis have been reported rarely.

OVERDOSAGE

Overdosage experience is limited. In one case report of overdose, abnormal liver function tests developed. These spontaneously reverted to normal when the drug was stopped. Clinical monitoring and supportive therapy should be employed. Pyrazinamide is dialyzable.^13

DOSAGE & ADMINISTRATION

Pyrazinamide should always be administered with other effective antituberculous drugs. It is administered for the initial 2 months of a 6-month or longer treatment regimen for drug-susceptible patients. Patients who are known or suspected to have drug-resistant disease should be treated with regimens individualized to their situation. Pyrazinamide frequently will be an important component of such therapy.

Patients with concomitant HIV infection may require longer courses of therapy. Physicians treating such patients should be alert to any revised recommendations from CDC for this group of patients.

Usual dose: Pyrazinamide is administered orally, 15 to 30 mg/kg once daily. Older regimens employed 3 to 4 divided doses daily, but most current recommendations are for once a day. Three grams per day should not be exceeded. The CDC recommendations do not exceed 2 g per day when given as a daily regimen (see table).

Alternatively, a twice weekly dosing regimen (50 to 70 mg/kg twice weekly based on lean body weight) has been developed to promote patient compliance with a regimen on an outpatient basis. In studies evaluating the twice weekly regimen, doses of pyrazinamide in excess of 3 g twice weekly have been administered. This exceeds the recommended maximum 3 g/daily dose. However, an increased incidence of adverse reactions has not been reported.

The table is taken from the CDC-American Thoracic Society joint recommendations:^4

Recommended Drugs for the Initial Treatment of Tuberculosis in Children and Adults

Drug | Daily Dose* |  | Maximal Daily Dose in Children and Adults | Twice Weekly Dose
Drug | Children | Adults | Maximal Daily Dose in Children and Adults | Children | Adults
Isoniazid | 10 to 20 mg/kg PO or IM | 5 mg/kg PO or IM | 300 mg | 20 to 40 mg/kg Max. 900 mg | 15 mg/kg Max. 900 mg
Rifampin | 10 to 20 mg/kg PO | 10 mg/kg PO | 600 mg | 10 to 20 mg/kg Max. 600 mg | 10 mg/kg Max. 600 mg
Pyrazinamide | 15 to 30 mg/kg PO | 15 to 30 mg/kg PO | 2 g | 50 to 70 mg/kg | 50 to 70 mg/kg
Streptomycin | 20 to 40 mg/kg IM | 15 mg/kg** IM | 1 g** | 25 to 30 mg/kg IM | 25 to 30 mg/kg IM
Ethambutol | 15 to 25 mg/kg PO | 15 to 25 mg/kg PO | 2.5 g | 50 mg/kg | 50 mg/kg

Definition of abbreviations: PO = perorally; IM = intramuscularly.

* Doses based on weight should be adjusted as weight changes.

**In persons older than 60 yrs of age the daily dose of streptomycin should be limited to 10 mg/kg with a maximal dose of 750 mg.

HOW SUPPLIED

Pyrazinamide Tablets, USP 500 mg are round, white, scored tablets, debossed "N" above the score and "484" below the score.

NDC 70954-484-10 - Bottle of 60

NDC 70954-484-20 - Bottle of 90

NDC 70954-484-30 - Bottle of 100

NDC 70954-484-40 - Bottle of 500

Store at 20° to 25°C (68° to 77°F) [See USP Controlled Room Temperature].

Dispense in a tight, light-resistant container as defined in the USP using a child-resistant closure.

REFERENCES

1. Drug Information, American Hospital Formulary Service. American Society of Hospital Pharmacists. Bethesda, MD. 1991.
2. USPDI, Drug Information for the Health Care Professional. United States Pharmacopeial Convention, Inc. Rockville, MD. 1991:1B:2226-2227.
3. Goodman-Gilman A, Rall TW, Nies AS, Taylor P. The Pharmacological Basis of Therapeutics, ed 8. New York, Pergamon Press. 1990;1154.
4. Treatment of tuberculosis and tuberculosis infection in adults and children. Am Rev Respir Dis. 1986;134:363-368.
5. Reynolds JEF, Parfitt K, Parsons AV, Sweetman SC. Martindale The Extra Pharmacopoeia, ed 29. London, The Pharmaceutical Press. 1989;569-570.
6. Bioassay of pyrazinamide for possible carcinogenicity. National Cancer Institute Carcinogenesis Technical Report Series No. 48, 1978.
7. Zerger E, Anderson B, Haworth S, Lawlor T, Mortelmans K, Speck W. Salmonella mutagenicity tests:III. Results from the testing of 255 chemicals. Environ Mutagen. 1987;9 (Suppl 9):1-109.
8. Roman IC, Georgian L. Cytogenetic effects of some antituberculosis drugs in vitro. Mutation Research. 1977;48:215-224.
9. Holdiness M. Antituberculosis drugs and breast-feeding. Arch Intern Med. 1984;144:1888.
10. Turcios N, Evans H. Preventing and managing tuberculosis in children. J Resp Dis. 1989;10(6)(Jun):23.
11. Starke JR. Multidrug therapy for tuberculosis in children. Pediatr Infec Dis J. 1990;9:785793.
12. Specific requirements on content and format of labeling for human prescription drugs; proposed addition of "geriatric use" subsection in the labeling. Federal Register. 1990;55(212)(Nov 1):46134-46137.
13. Stamathakis G, Montes C, Trouvin JH, et al. Pyrazinamide and pyrazinoic acid pharmacokinetics in patients with chronic renal failure. Clinical Nephrology. 1988;30:230-234.

All trademarks are the property of their respective owners.

Manufactured by:

Novitium Pharma, LLC

70 Lake Drive, East Windsor

New Jersey 08520

Issued: 01/2021

LB4280-00

PACKAGE LABEL.PRINCIPAL DISPLAY PANEL

Pyrazinamide Tablets, USP 500 mg
70954-484-10 - Bottle of 60

Pyrazinamide Tablets, USP 500 mg
70954-484-20 - Bottle of 90

Pyrazinamide Tablets, USP 500 mg
70954-484-30 - Bottle of 100